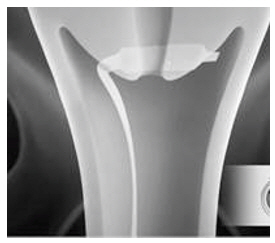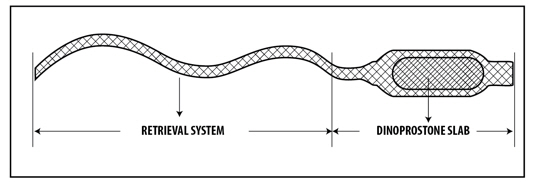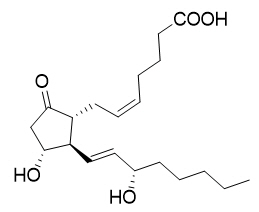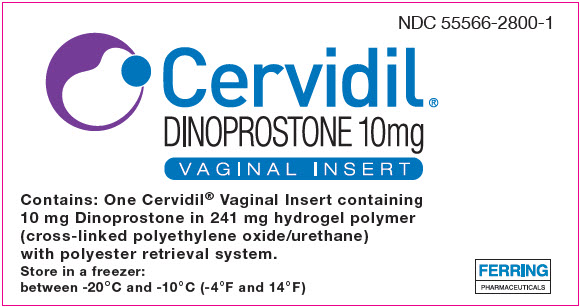 DRUG LABEL: CERVIDIL
NDC: 55566-2800 | Form: INSERT
Manufacturer: Ferring Pharmaceuticals Inc.
Category: prescription | Type: HUMAN PRESCRIPTION DRUG LABEL
Date: 20230602

ACTIVE INGREDIENTS: DINOPROSTONE 10 mg/241 mg
INACTIVE INGREDIENTS: POLYETHYLENE GLYCOL, UNSPECIFIED

HIGHLIGHTS OF PRESCRIBING INFORMATION

These highlights do not include all the information needed to use CERVIDIL safely and effectively. See full prescribing information for CERVIDIL.
CERVIDIL® (dinoprostone) vaginal insert
Initial U.S. Approval: 1977

1 INDICATIONS AND USAGE

CERVIDIL is a prostaglandin analog indicated for the initiation and/or continuation of cervical ripening in pregnant women at or near term in whom there is a medical or obstetrical indication for the induction of labor. (1)

2 DOSAGE AND ADMINISTRATION

- Administer a single vaginal insert (10 mg) for up to 12 hours of use (approximately 0.3 mg of dinoprostone is released per hour) (2.1)
- Remove upon onset of active labor or 12 hours after insertion. (2.1)
- Carefully monitor for uterine activity, fetal status and the progression of cervical dilatation and effacement. (2.1)
- CERVIDIL should be administered only by trained obstetrical personnel in a hospital setting with appropriate obstetrical care facilities (2.2).
- See full prescribing information for complete preparation, administration, and removal instructions. (2.2, 2.3)

3 DOSAGE FORMS AND STRENGTHS

Vaginal Insert: 10 mg of dinoprostone contained within a knitted polyester pouch retrieval system. (3)

4 CONTRAINDICATIONS

CERVIDIL is contraindicated for:

- Known hypersensitivity to prostaglandins (4)
- Evidence or clinical suspicion of fetal distress, where delivery is not imminent (4)
- Unexplained vaginal bleeding in the current pregnancy (4)
- Evidence or clinical suspicion of marked cephalopelvic disproportion (4)
- Contraindication to induction of labor (4)
- Concurrent use with intravenous oxytocic agents (4)
- History of previous cesarean section or other uterine surgery (such as myomectomy) (4)
- Conditions under which prolonged contraction of the uterus may be detrimental to fetal safety. (4)
- Six or more previous term pregnancies (4)

5 WARNINGS AND PRECAUTIONS

- Disseminated Intravascular Coagulation: Assess for evolving fibrinolysis in the immediate post-partum period. (5.2)
- Amniotic Fluid Embolism Syndrome: Carefully monitor patients for clinical signs of hypotension, hypoxemia and respiratory failure, DIC, coma or seizures. Provide supportive care. (5.3)
- Uterine Tachysystole and Uterine Hypersystole/Hypertonicity: Monitor uterine activity; remove vaginal insert. (5.4)
- History of Glaucoma: Consider non-prostaglandin cervical ripening procedures. (5.5)

6 ADVERSE REACTIONS

The most common adverse reactions (≥ 2 %) are uterine tachysystole without fetal distress, uterine tachysystole with fetal distress, and fetal distress without uterine tachysystole. (6.1)

To report SUSPECTED ADVERSE REACTIONS, contact FERRING PHARMACEUTICALS, INC. at 1 888-FERRING (1-888-337-7464) or FDA at 1-800-FDA-1088 or www.fda.gov/medwatch.

7 DRUG INTERACTIONS

Oxytocic Agents: May augment the activity of oxytocic agents; concomitant use of intravenous oxytocic agents is contraindicated (4, 7.1). Remove vaginal insert at least 30 minutes before administering an oxytocic agent. (7.1)

FULL PRESCRIBING INFORMATION

1 INDICATIONS AND USAGE

CERVIDIL is indicated for the initiation and/or continuation of cervical ripening in pregnant women at or near term in whom there is a medical or obstetrical indication for the induction of labor.

2 DOSAGE AND ADMINISTRATION

2.1 Dosage Instructions

Administer one CERVIDIL insert (10 mg) intravaginally for use up to 12 hours (approximately 0.3 mg of dinoprostone is released per hour) [see Dosage and Administration (2.2)].

Monitor uterine activity, fetal status, and the progression of cervical dilatation and effacement with the use of CERVIDIL. Remove CERVIDIL 12 hours after insertion with the onset of active labor, prior to an amniotomy, occurrence of uterine tachysystole, uterine hypersystole/hypertonicity, or fetal distress [see Warnings and Precautions (5.4)]. Remove CERVIDIL at least 30 minutes prior to administering an oxytocic agent [see Warnings and Precautions (5.4) and Drug Interactions (7)].

2.2 Preparation and Administration Instructions

CERVIDIL should be administered only by trained obstetrical personnel in a hospital setting with appropriate obstetrical care facilities.

Preparation and Administration Instructions

- Keep CERVIDIL frozen until ready for use. Do not warm CERVIDIL prior to vaginal insertion.
- Tear open the individually-wrapped foil package containing CERVIDIL along the tear mark. Never open the package using scissors or other sharp objects because this may damage the knitted polyester retrieval system. Do not cut the retrieval system and do not use CERVIDIL unless its retrieval system is intact.
- Immediately after opening the package, insert CERVIDIL transversely, in the posterior fornix of the vagina (see Figure 1). If necessary, use a minimal amount of water-miscible lubricant to assist vaginal insertion. Do not permit excess contact or coating with the lubricant, as this could prevent release of dinoprostone from the vaginal insert. Insertion does not require sterile conditions.
  Figure 1: Placement of CERVIDIL in the Posterior Vaginal Fornix
- Tuck some of the excess retrieval system into the vagina to avoid movement of CERVIDIL away from the proper position; however, leave a small amount of the retrieval system outside the vagina to aid in retrieval.
- Instruct women to remain in a recumbent position during insertion of CERVIDIL and for 2 hours afterward. Women may be ambulatory 2 hours after insertion; however, ensure that the insert remains in place.

2.3 Removal Instructions

- To retrieve, locate the retrieval system and pull it gently until CERVIDIL is fully removed.
- Upon removal of CERVIDIL, it is essential to perform a visual inspection to ensure that the slab has been removed, as it will continue delivering the active ingredient.

3 DOSAGE FORMS AND STRENGTHS

Vaginal Insert: 10 mg of dinoprostone (release rate approximately 0.3 mg/hour up to 12 hours) in a hydrogel polymer. The insert is beige-colored, semi-opaque, thin, flat, and rectangular in shape with rounded corners, measuring 29 mm by 9.5 mm by 0.8 mm, contained within an off-white knitted polyester pouch retrieval system (see Figure 2).

Figure 2: CERVIDIL Components

4 CONTRAINDICATIONS

CERVIDIL is contraindicated in patients with:

- Known hypersensitivity to prostaglandins [see Adverse Reactions (6.2)]
- Evidence or clinical suspicion of fetal distress where delivery is not imminent
- Unexplained vaginal bleeding in the current pregnancy
- Evidence or clinical suspicion of marked cephalopelvic disproportion
- Conditions for which induction of labor is contraindicated
- Conditions for which oxytocic drugs are contraindicated
- Previous cesarean section or other uterine surgery expected to affect uterine integrity (such as myomectomy)
- Conditions under which prolonged contraction of the uterus may be detrimental to fetal safety
- Concurrent use with intravenous oxytocic agents [see Warnings and Precautions (5.4) and Drug Interactions (7)]
- Six or more previous term pregnancies

5 WARNINGS AND PRECAUTIONS

5.1 For Hospital Use Only

CERVIDIL should be administered in a hospital setting with an obstetrical care facility.

5.2 Disseminated Intravascular Coagulation

CERVIDIL should be used with caution in women at high risk of postpartum disseminated intravascular coagulation (DIC). Physiologic or pharmacologic induction of labor, including the use of CERVIDIL, is associated with an increased risk of DIC during the postpartum period. Women aged 30 years or older, those with complications during pregnancy and those with a gestational age over 40 weeks have an increased risk of DIC during the postpartum period. As soon as possible, assess for an evolving fibrinolysis in the immediate post-partum period. Therapy consisting of prompt removal of the source of procoagulant material, replacement of depleted clotting factors and, in some cases, anti-coagulation with heparin should be instituted promptly.

5.3 Amniotic Fluid Embolism Syndrome

The use of dinoprostone-containing products, including CERVIDIL, can result in inadvertent disruption and subsequent embolization of antigenic tissue causing the development of Amniotic Fluid Embolism Syndrome, a rare and often fatal obstetric condition.

Carefully monitor patients for clinical signs of Amniotic Fluid Embolism Syndrome including hypotension, hypoxemia and respiratory failure, DIC, coma or seizures and provide supportive care as needed.

5.4 Uterine Tachysystole and Uterine Hypersystole/Hypertonicity

The use of CERVIDIL may cause uterine tachysystole with or without fetal heart rate changes (see Table 1). While using CERVIDIL, carefully monitor uterine activity, fetal status and the progression of cervical dilatation and effacement. Remove CERVIDIL with any evidence of uterine tachysystole, uterine hypersystole/hypertonicity, fetal distress, or if labor commences. CERVIDIL is contraindicated when prolonged contraction of the uterus is detrimental to fetal safety or uterine integrity, such as previous cesarean section or major uterine surgery, because of the risk of uterine rupture and obstetrical complications (e.g., need for hysterectomy and the occurrence of fetal or neonatal death). Prostaglandins, including CERVIDIL, may potentiate the effect of oxytocin [see Drug Interactions (7)]. Remove CERVIDIL at least 30 minutes before administration of an oxytocic agent is initiated and continue to carefully monitor uterine activity. Remove CERVIDIL prior to amniotomy or following rupture of membranes because the higher vaginal pH that occurs with rupture of membranes may result in higher release rate of dinoprostone.

5.5 Glaucoma

Prostaglandins, including CERVIDIL, can lead to raised intraocular pressure and constriction of pupils. Consider non-prostaglandin cervical ripening procedures in patients with Glaucoma.

6 ADVERSE REACTIONS

The following adverse reactions are described, or described in greater detail, in other sections:

- Disseminated Intravascular Coagulation [see Warnings and Precautions (5.2)]
- Amniotic Fluid Embolism [see Warnings and Precautions (5.3)]
- Uterine Tachysytole and Uterine Hypersystole/Hypertonicity [see Warnings and Precautions (5.4)]

6.1 Clinical Trials Experience

Because clinical trials are conducted under widely varying conditions, adverse reaction rates observed in the clinical trials of a drug cannot be directly compared to rates in the clinical trials of another drug and may not reflect the rates observed in practice.

In placebo-controlled trials of 658 pregnant women (320 CERVIDIL-treated women and 338 placebo-treated women), the following treatment related adverse reactions (see Table 1) occurred at an incidence greater than 2% (and greater than that reported in the placebo group) in the CERVIDIL group [see Clinical Studies (14)].

Table 1. Common Adverse Reactions (≥ 2%) in Pregnant Patients Near Term Gestation in Trial 1 [Trial 1 (101-103) and Trial 2 (101-003) evaluated the dinoprostone insert only, without the use of a retrieval system] , Trial 2, and Trial 3 [Trial 3 (101-801) evaluated the dinoprostone insert with the retrieval system.]
 | Trials 1and 2
 | CERVIDIL (N=320) | Placebo (N=338)
Uterine tachysystole with fetal distress | 2.8% | 0.3%
Uterine tachysystole without fetal distress | 4.7% | 0%
Fetal distress without uterine tachysystole - | 3.8% | 1.2%
 | Trial 3
 | CERVIDIL (N=102) | Placebo (N=104)
Uterine tachysystole with fetal distress | 2.9% | 0%
Uterine tachysystole -without fetal distress | 2% | 0%
Fetal distress without uterine tachysystole | 2.9% | 1%

Drug related fever, nausea, vomiting, diarrhea, and abdominal pain occurred in less than 1% of CERVIDIL-treated patients.

In Trial 3 (with the retrieval system) cases of tachysystole uterine hyperstimulation reversed within 2 to 13 minutes of removal of CERVIDIL. Tocolytics were required in one of the five cases.

6.2 Postmarketing Experience

The following adverse reactions have been identified during postapproval use of CERVIDIL or other dinoprostone products. Because these reactions are reported voluntarily from a population of uncertain size, it is not always possible to reliably estimate their frequency or establish a causal relationship to drug exposure.

Blood and lymphatic system disorders: Disseminated Intravascular Coagulation

Cardiovascular disorders: Myocardial Infarction in women with a history of myocardial infarction

Immune system disorders: Hypersensitivity

Nervous system disorders: Headache

Pregnancy, puerperium and perinatal conditions: Amniotic fluid embolism

Reproductive system: reports of uterine rupture have been reported in association with use of CERVIDIL. Some required a hysterectomy and others resulted in subsequent fetal or neonatal death. Uterine hypertonus

Vascular disorders: Hypotension

7 DRUG INTERACTIONS

7.1 Oxytocic Agents

CERVIDIL is contraindicated in patients receiving intravenous oxytocic agents because CERVIDIL may augment the activity of oxytocic agents. A dosing interval of at least 30 minutes is recommended for the sequential use of an oxytocic agent following the removal of CERVIDIL.

8 USE IN SPECIFIC POPULATIONS

8.1 Pregnancy

Risk Summary

CERVIDIL is indicated for the initiation and/or continuation of cervical ripening in pregnant women at or near term in whom there is a medical or obstetrical indication for the induction of labor. Fetal, neonatal, and maternal risks are discussed throughout the labeling. Limited available data with CERVIDIL use in pregnant women do not show a clear association with adverse developmental outcomes. Relevant animal reproduction data with dinoprostone is not available.

Data

Human Data

In a report of a 3-year pediatric follow-up study, there were no deleterious effects noted on physical examination or psychomotor evaluation of 51 infants born following maternal treatment with CERVIDIL.

Clinical Considerations

Fetal/Neonatal Adverse Reactions

When CERVIDIL was removed for fetal distress, there was a return to normal rhythm and there were no neonatal sequelae. Remove CERVIDIL in the event of persistent tachysystole with or without fetal heart rate changes, and follow established institutional protocols in management of patients.

8.2 Lactation

Risk Summary

Concomitant administration of CERVIDIL is not indicated in breastfeeding women. There is no information on the effects of maternal CERVIDIL administration on the breastfed child. Insufficient information is available on the effects of maternal CERVIDIL administration on milk production.

8.4 Pediatric Use

The safety and effectiveness of CERVIDIL have not been established in pregnant girls.

11 DESCRIPTION

CERVIDIL (dinoprostone) vaginal insert contains dinoprostone, a prostaglandin analog. Each vaginal insert contains 10 mg of dinoprostone in 241 mg of a cross-linked polyethylene oxide/urethane polymer (hydrogel polymer) that is semi-opaque, beige colored, flat, rectangular in shape with rounded corners and measuring 29 mm by 9.5 mm by 0.8 mm. The vaginal insert is contained within a pouch of an off-white knitted polyester yarn retrieval system. When placed in a moist environment, the yarn absorbs water, swells, and releases the enclosed dinoprostone. The knitted polyester retrieval system has a long tape-like end that is designed to aid retrieval of CERVIDIL at the end of the dosing interval or earlier if clinically indicated. The finished product is a controlled-release formulation that has been found to release dinoprostone in vivo at a rate of approximately 0.3 mg per hour.

The chemical name for dinoprostone (known as prostaglandin E2 or PGE2) is 11α,15S-dihydroxy-9-oxo-prosta-5Z,13E-dien-1-oic acid and the structural formula is represented below:

The molecular formula is C20H32O5 and its molecular weight is 352.47. Dinoprostone occurs as a white to off-white crystalline powder. It has a melting point within the range of 65° to 69°C. Dinoprostone is soluble in ethanol and in 25% ethanol in water.

12 CLINICAL PHARMACOLOGY

12.1 Mechanism of Action

Dinoprostone is found in low concentrations in most tissues of the body and functions as a local hormone. In pregnancy, dinoprostone is secreted continuously by the fetal membranes and placenta and plays an important role in the final events leading to the initiation of labor including cervical ripening. Dinoprostone stimulates the production of prostaglandin F2α (PGF2α), which sensitizes the myometrium to endogenous or exogenously administered oxytocin. Available evidence indicates that dinoprostone, in the concentrations found during the early part of labor, plays an important role in cervical ripening without affecting uterine contractions.

In most patients, local effects of CERVIDIL on the cervix include changes in the tissue consistency, dilatation and effacement. Some women experience systemic effects, including uterine tachysystole, and uterine hypersystole/hypertonicity, as a result dinoprostone or PGF2α mediated sensitization of the myometrium to oxytocin [see Warnings and Precautions (5.4)].

12.2 Pharmacodynamics

No specific pharmacodynamic studies were conducted with CERVIDIL.

12.3 Pharmacokinetics

The delivery rate of dinoprostone from CERVIDIL in vivo is approximately 0.3 mg/per hour over a period of 12 hours. Dinoprostone is metabolized in the tissues of synthesis with the half-life estimated to be 2.5 to 5 minutes. The rate limiting step for inactivation is regulated by the enzyme 15-hydroxyprostaglandin dehydrogenase (PGDH). Any dinoprostone that escapes local inactivation is cleared to the extent of 95% on the first pass through the pulmonary circulation.

No correlation could be established between the release of dinoprostone from CERVIDIL and plasma concentrations of metabolite of dinoprostone (PGEm). The relative contributions of endogenously and exogenously released dinoprostone to the plasma levels of the metabolite PGEm is not known.

13 NONCLINICAL TOXICOLOGY

13.1 Carcinogenesis, Mutagenesis, Impairment of Fertility

Long-term carcinogenicity and fertility studies have not been conducted with dinoprostone. No evidence of mutagenicity has been observed with dinoprostone in the Unscheduled DNA Synthesis Assay, the Micronucleus Test, or the bacteria reverse mutation (Ames) test.

14 CLINICAL STUDIES

The effectiveness and safety of CERVIDIL for the induction of cervical ripening was evaluated in 658 pregnant women (320 CERVIDIL-treated women and 338 placebo-treated women) at or near term in three randomized, double-blind, placebo-controlled trials (Trials 1, 2, and 3). Efficacy outcomes included percentage with treatment success (defined as vaginal delivery within 12 hours, Bishop Score ≥ 6 in the 12-hour observation period, or ≥ 3 increase in the Bishop score in the 12-hour observation period), time to delivery, and time to onset of labor. Table 2 presents efficacy outcomes from Trials 1, 2, and 3.

Table 2: Efficacy Outcomes in Pregnant Women in Trials 1 [Trial 1 and Trial 2 evaluated the dinoprostone insert only, without the use of a retrieval system.] , 2, and 3 [Trial 3 evaluated the dinoprostone insert with the retrieval system] for CERVIDIL Ripening, Intent-to-Treat Population
 | Primipara/Nullipara |  | Multipara
Study # | CERVIDIL | Placebo | CERVIDIL | Placebo | P-Value
Treatment Success [Treatment success was defined as vaginal delivery within 12 hours, Bishop score ≥ 6 in the 12-hour observation period, or ≥ 3 increase in the Bishop score in the 12-hour observation period.]
Trial 1 (N=81) | 65% (n=26) | 28% (n=32) | 87% (n=16) | 29% (n=7) | <0.001
Trial 2 (N=371) | 68% (n=111) | 24% (n=123) | 77% (n=65) | 24% (n=72) | <0.001
Trial 3 (N=206) | 72% (n=60) | 48% (n=63) | 55% (n=42) | 41% (n=41) | 0.003
Median Time to Delivery (hours)
Trial 1 (N=81) | 25.7 (n=26) | 34.5 (n=32) | 12.3 (n=16) | 24.6 (n=7) | 0.001
Trial 3 (N=206) | 25.5 (n=60) | 37.2 (n=63) | 20.8 (n=42) | 27.4 (n=41) | <0.001
Median Time to Onset of Labor (hours)
Trial 1 (N=81) | 12 (n=26) | 19.2 (n=32) | 6.9 (n=16) | 18.3 (n=7) | <0.001

16 HOW SUPPLIED/STORAGE AND HANDLING

How Supplied

CERVIDIL vaginal insert contains 10 mg dinoprostone in a hydrogel polymer (NDC 55566-2800-1). The vaginal insert is beige-colored, semi-opaque, thin, flat, and rectangular in shape with rounded corners, measuring 29 mm by 9.5 mm by 0.8 mm, and is contained within an off-white knitted polyester pouch retrieval system.

CERVIDIL is enclosed in an aluminum/polyethylene pack.

Storage and Handling

Store in a freezer between -20°C and -10°C (-4°F and 14°F). CERVIDIL, enclosed in its aluminum/polyethylene pack, is stable when stored in a freezer for a period of three years. Vaginal inserts exposed to high humidity will absorb moisture from the air and thereby alter the release characteristics of dinoprostone.

17 PATIENT COUNSELING INFORMATION

Administration

Advise the woman to remain in the recumbent position for 2 hours following CERVIDIL insertion and to inform her health care provider immediately if CERVIDIL does not remain in place [see Dosage and Administration (2.2)].

Disseminated Intravascular Coagulation

Inform women that the use of CERVIDIL is associated with an increased risk of disseminated intravascular coagulation (DIC) during the postpartum period [see Warnings and Precautions (5.2)].

Amniotic Fluid Embolism Syndrome

Inform women that the use of CERVIDIL can result in inadvertent disruption and subsequent embolization of antigenic tissue causing the development of Amniotic Fluid Embolism Syndrome, a rare and often fatal obstetric condition [see Warnings and Precautions (5.3)].

Frequent or Prolonged Uterine Contractions

Inform women that the use of CERVIDIL may cause frequent or prolonged contractions [see Warnings and Precautions (5.4)]. This might result in disruption of blood flow through the placenta and to the fetus.

Glaucoma

Inform women that CERVIDIL can lead to raised intraocular pressure and constriction of pupils [see Warnings and Precautions (5.5)].

Manufactured for:
Ferring Pharmaceuticals, Inc.
Parsippany, NJ 07054

PRINCIPAL DISPLAY PANEL - 10 mg Pouch Carton

NDC 55566-2800-1

Cervidil®
DINOPROSTONE 10mg
VAGINAL INSERT

Contains: One Cervidil® Vaginal Insert containing
10 mg Dinoprostone in 241 mg hydrogel polymer
(cross-linked polyethylene oxide/urethane)
with polyester retrieval system.

Store in a freezer:
between -20°C and -10°C (-4°F and 14°F)

FERRING
PHARMACEUTICALS